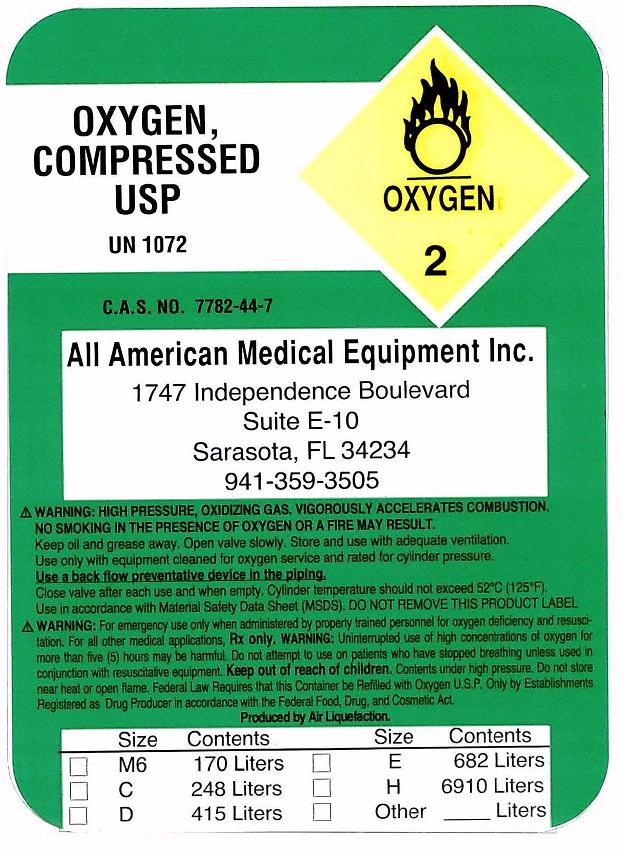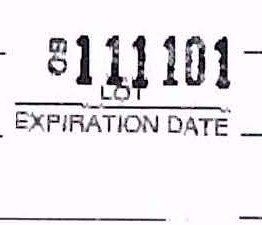 DRUG LABEL: Oxygen
NDC: 68685-0001 | Form: GAS
Manufacturer: All American Medical Equipment, Inc. 
Category: prescription | Type: HUMAN PRESCRIPTION DRUG LABEL
Date: 20091120

ACTIVE INGREDIENTS: Oxygen 99 L/100 L

Oxygen